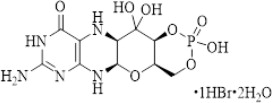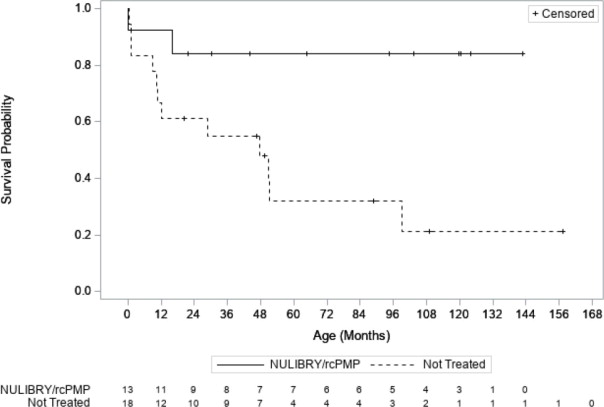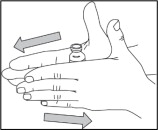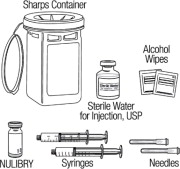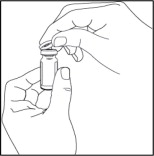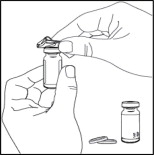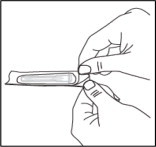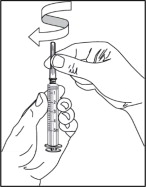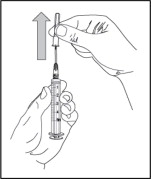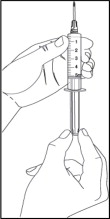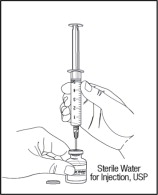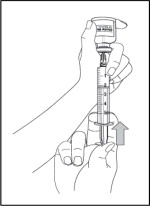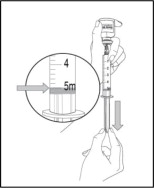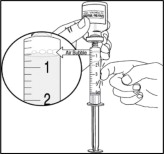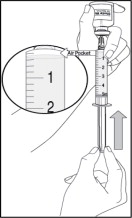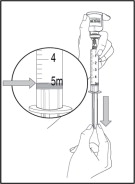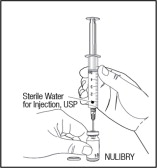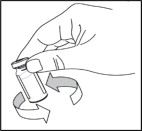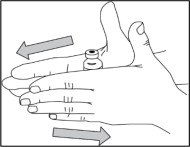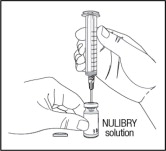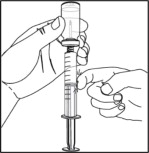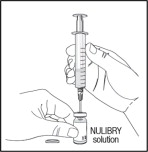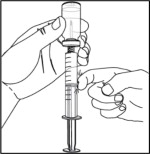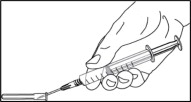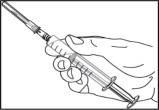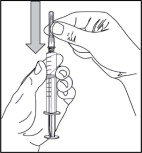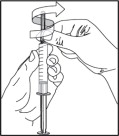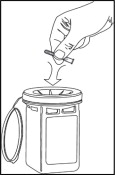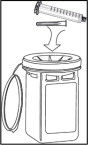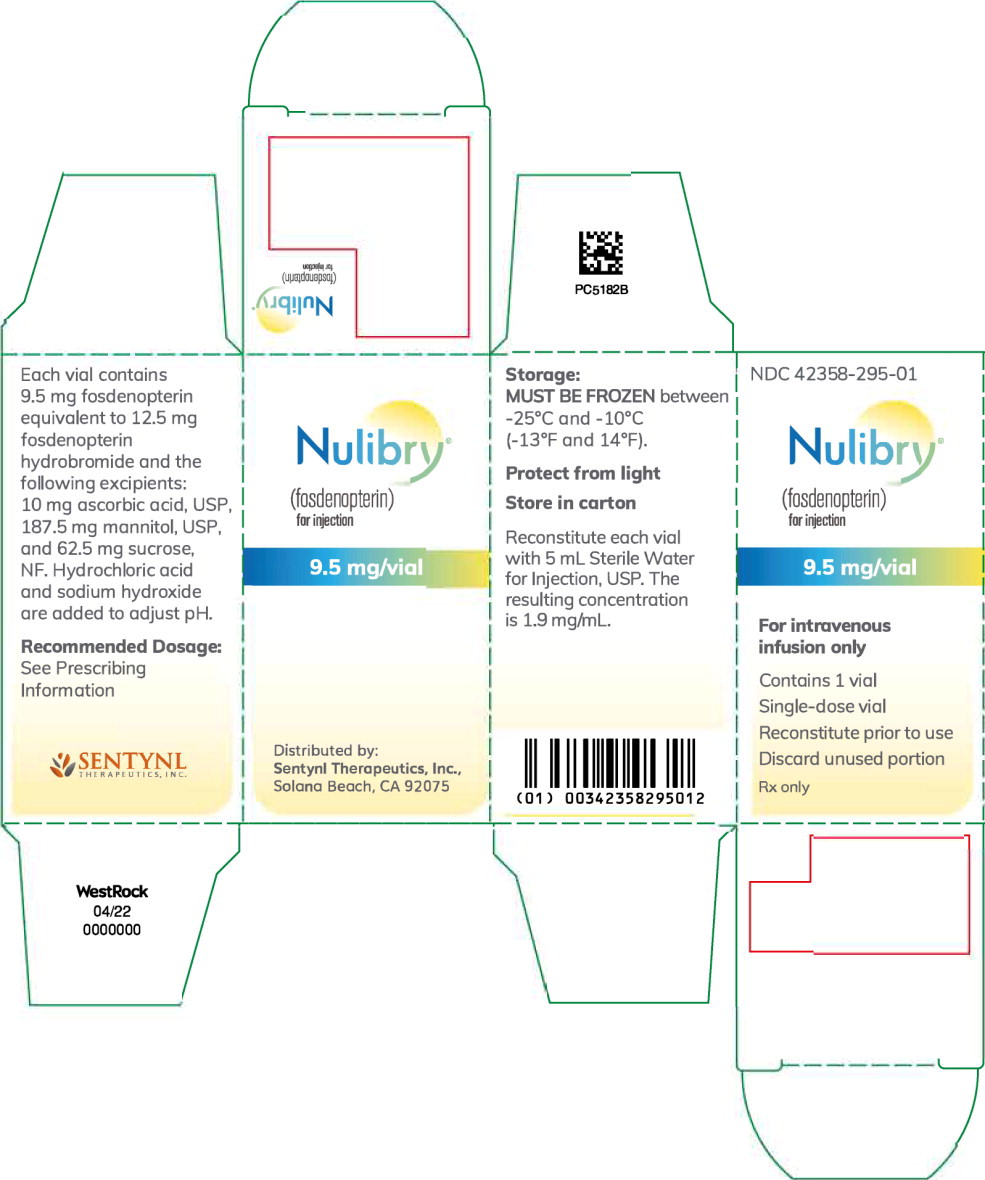 DRUG LABEL: Nulibry
NDC: 42358-295 | Form: INJECTION, POWDER, LYOPHILIZED, FOR SOLUTION
Manufacturer: Sentynl Therapeutics, Inc.
Category: prescription | Type: HUMAN PRESCRIPTION DRUG LABEL
Date: 20221028

ACTIVE INGREDIENTS: fosdenopterin hydrobromide 9.5 mg/1 1
INACTIVE INGREDIENTS: mannitol 187.5 mg/1 1; sucrose 62.5 mg/1 1; ascorbic acid 10 mg/1 1; hydrochloric acid; sodium hydroxide

HIGHLIGHTS OF PRESCRIBING INFORMATION

These highlights do not include all the information needed to use NULIBRY® safely and effectively. See full prescribing information for NULIBRY.
NULIBRY (fosdenopterin) for injection, for intravenous use
Initial U.S. Approval: 2021

1 INDICATIONS AND USAGE

NULIBRY is cyclic pyranopterin monophosphate (cPMP) indicated to reduce the risk of mortality in patients with molybdenum cofactor deficiency (MoCD) Type A. (1)

2 DOSAGE AND ADMINISTRATION

- Start NULIBRY if known or presumed MoCD Type A. Promptly discontinue if MoCD Type A is not confirmed by genetic testing. (2.1)
- Reconstitute before use and complete infusion within 4 hours of reconstitution. (2.2, 2.4)
- Administer as an intravenous infusion once daily at a rate of 1.5 mL/minute with non-DEHP tubing with a 0.2 micron filter. Volumes below 2 mL may require syringe administration through slow intravenous push. (2.2)
- See Full Prescribing Information for additional important preparation instructions and administration instructions. (2.2)
- See the table below for the recommended dosage in patients less than one year of age. (2.3)

Titration Schedule | Preterm Neonates (Gestational Age Less than 37 Weeks) | Term Neonates (Gestational Age 37 weeks and Above)
Initial Dosage | 0.4 mg/kg once daily | 0.55 mg/kg once daily
Month 1 | 0.7 mg/kg once daily | 0.75 mg/kg once daily
Month 3 | 0.9 mg/kg once daily | 0.9 mg/kg once daily

Recommended Dosage in Patients One Year of Age or Older: 0.9 mg/kg given as an intravenous infusion once daily. (2.3)

3 DOSAGE FORMS AND STRENGTHS

For injection: 9.5 mg of fosdenopterin as a lyophilized powder or cake in a single-dose vial for reconstitution. (3)

4 CONTRAINDICATIONS

None. (4)

5 WARNINGS AND PRECAUTIONS

Potential for Photosensitivity: Advise patients/caregivers to avoid patient exposure to sunlight, and to have the patient wear sunscreen, protective clothing, and sunglasses when exposed to the sun. If photosensitivity occurs, advise caregivers/patients to seek medical attention immediately and consider a dermatological evaluation. (5.1, 13.2)

6 ADVERSE REACTIONS

The most common adverse reactions (>25%) were catheter-related complications, pyrexia, viral infection, pneumonia, otitis media, vomiting, cough/sneezing, viral upper respiratory infection, gastroenteritis, bacteremia, and diarrhea. (6.1)

To report SUSPECTED ADVERSE REACTIONS, contact Sentynl Therapeutcis, Inc. at 888-507-5206 or FDA at
1-800-FDA-1088 or www.fda.gov/medwatch.

FULL PRESCRIBING INFORMATION

1 INDICATIONS AND USAGE

NULIBRY is indicated to reduce the risk of mortality in patients with molybdenum cofactor deficiency (MoCD) Type A.

2 DOSAGE AND ADMINISTRATION

2.1 Patient Selection

Start NULIBRY if the patient has a diagnosis or presumptive diagnosis of MoCD Type A.

In patients with a presumptive diagnosis of MoCD Type A, confirm the diagnosis of MoCD Type A immediately after initiation of NULIBRY treatment. In such patients, discontinue NULIBRY if the MoCD Type A diagnosis is not confirmed by genetic testing.

2.2 Important Administration Information

- NULIBRY is intended for administration by a healthcare provider. If deemed appropriate by a healthcare provider, NULIBRY may be administered at home by the patient's caregiver. If NULIBRY can be administered by a caregiver/patient, advise them to read the detailed instructions on the preparation, administration, storage, and disposal of NULIBRY for caregivers [see Instructions for Use].
- NULIBRY is for intravenous infusion only. Administer with non-DEHP tubing with a 0.2 micron filter. Do not mix NULIBRY with other drugs (note NULIBRY is reconstituted with Sterile Water for Injection, USP). Do not administer as an infusion with other drugs.
- NULIBRY is given through an infusion pump at a rate of 1.5 mL per minute.
- Dose volumes below 2 mL may require syringe administration through slow intravenous push.
- Administration of NULIBRY must be completed within 4 hours of reconstitution [see Dosage and Administration (2.5)].

2.3 Recommended Dosage and Administration

Recommended Dosage and Administration in Patients Less Than One Year of Age (by gestational age)

The recommended dosage regimen of NULIBRY in patients less than one year of age (by gestational age) is based on actual body weight as shown in Table 1.

Table 1 Recommended Initial Dosage and Titration Schedule of NULIBRY for Patients Less Than One Year of Age by Gestational Age
Titration Schedule | Preterm Neonates (Gestational Age Less than 37 Weeks) | Term Neonates (Gestational Age 37 Weeks and Above)
Initial Dosage | 0.4 mg/kg once daily | 0.55 mg/kg once daily
Dosage at Month 1 | 0.7 mg/kg once daily | 0.75 mg/kg once daily
Dosage at Month 3 | 0.9 mg/kg once daily | 0.9 mg/kg once daily

Recommended Dosage and Administration in Patients One Year of Age or Older

For patients one year of age or older, the recommended dosage of NULIBRY is 0.9 mg/kg (based on actual body weight) administered as an intravenous infusion once daily.

Recommendations for a Missed Dose

If a NULIBRY dose is missed, administer the missed dose as soon as possible. Administer the next scheduled dose at least 6 hours after the administration of the missed dose.

2.4 Preparation and Administration Instructions

NULIBRY must be reconstituted prior to use. Use aseptic technique during preparation and follow these instructions:

1. Determine the total dose, number of vials needed, and total reconstituted dose volume based on the patient's weight and prescribed dose.
2. Remove the required number of vials from the freezer to allow them to reach room temperature (by hand warming for 3 to 5 minutes or exposing to ambient air for approximately 30 minutes).
3. Reconstitute each required NULIBRY vial with 5 mL of Sterile Water for Injection, USP. Gently swirl the vial continuously until the powder is completely dissolved. DO NOT shake. After reconstitution, the final concentration of NULIBRY reconstituted solution is 9.5 mg/5 mL (1.9 mg/mL).
4. Parenteral drug products should be inspected visually for particulate matter and discoloration prior to administration, whenever solution and container permit. Reconstituted NULIBRY is a clear and colorless to pale yellow solution. Do not use if there are particles present or if the solution is discolored.
5. Administer the total reconstituted dose.

2.5 Storage of Reconstituted Solution

Reconstituted NULIBRY may be stored at room temperature [15°C to 25°C (59°F to 77°F)] or refrigerated [2°C to 8°C (36°F to 46°F)] for up to 4 hours including infusion time. If reconstituted NULIBRY is refrigerated, allow it to come to room temperature (by hand warming for 3 to 5 minutes or exposing to ambient air for approximately 30 minutes) before administration. Do not heat. Do not re-freeze NULIBRY after reconstitution. Do not shake.

Discard all unused reconstituted NULIBRY solution 4 hours after reconstitution.

3 DOSAGE FORMS AND STRENGTHS

For injection: 9.5 mg of fosdenopterin, as a white to pale yellow lyophilized powder or cake in a single-dose vial for reconstitution.

4 CONTRAINDICATIONS

None.

5 WARNINGS AND PRECAUTIONS

5.1 Potential for Photosensitivity

Animal studies have identified that NULIBRY has phototoxic potential [see Nonclinical Toxicology (13.2)].

Advise NULIBRY-treated patients or their caregivers to avoid or minimize patient exposure to direct sunlight and artificial UV light exposure (i.e., UVA or UVB phototherapy) and adopt precautionary measures (e.g., have the patient wear protective clothing and hats, use broad spectrum sunscreen with high sun protection factor (SPF) in patients 6 months of age and older, and wear sunglasses when exposed to the sun). If photosensitivity occurs, advise caregivers/patients to seek medical attention immediately and consider a dermatological evaluation.

6 ADVERSE REACTIONS

6.1 Clinical Trials Experience

Because clinical trials are conducted under widely varying conditions, adverse reaction rates observed in the clinical trials of a drug cannot be directly compared to rates in the clinical trials of another drug and may not reflect the rates observed in practice.

Overview of Safety Evaluation

The safety of NULIBRY was assessed in 37 pediatric patients and healthy adults who received at least one intravenous infusion of NULIBRY or an E. coli derived non-salt, anhydrous form of cPMP (recombinant cPMP or rcPMP, which has the same active moiety and therefore the same biologic activity as NULIBRY). Of these 37 patients/healthy adults, 13 were pediatric patients with MoCD Type A in Studies 1, 2, and 3 [see Clinical Studies (14)], 6 were pediatric patients with presumptive MoCD Type A but who were later confirmed to not have MoCD Type A, and 18 were healthy adults (without MoCD Type A) in a Phase 1 study.

Adverse Reactions

Assessment of adverse reactions for NULIBRY is based on data from two open-label, single-arm studies, Study 1 (n=8) and Study 2 (n=1), in patients with a confirmed diagnosis of MoCD Type A (8 of the 9 patients were previously treated with rcPMP). In these studies, patients received a daily intravenous infusion of NULIBRY. The median exposure to NULIBRY was
4.3 years and ranged from 8 days to 5.6 years [see Clinical Studies (14)]. In these studies, 44% of patients were males and 56% were females, 67% were White and 33% were Asian. The mean age was 14 days and ranged from 1 day to 69 days at time of first infusion.

Table 2 presents the most common adverse reactions that occurred in NULIBRY-treated patients in Studies 1 and 2.

Table 2 Common Adverse Reactions Reported in Two or More NULIBRY-Treated Patients with MoCD Type A (Studies 1 and 2)
Adverse Reactions | NULIBRY-Treated Patients (N=9) n (%)
Catheter-related complications^1 | 8 (89%)
Pyrexia | 7 (78%)
Viral infection | 5 (56%)
Pneumonia | 4 (44%)
Otitis Media | 4 (44%)
Vomiting | 4 (44%)
Cough/Sneezing | 4 (44%)
Upper viral respiratory infection | 3 (33%)
Gastroenteritis | 3 (33%)
Diarrhea | 3 (33%)
Bacteremia | 3 (33%)
Abdominal pain | 2 (22%)
Influenza | 2 (22%)
Lower respiratory tract infection | 2 (22%)
Viral tonsillitis | 2 (22%)
Oropharyngeal pain | 2 (22%)
Rash maculo-papular | 2 (22%)
Anemia | 2 (22%)
Eye swelling | 2 (22%)
Seizure | 2 (22%)
Agitation | 2 (22%)
Abbreviations: MoCD = molybdenum cofactor deficiency
^1 Catheter-related complications included complication associated with device, catheter site abscess, catheter site discharge, catheter site extravasation, catheter site pain, catheter site infection, catheter site inflammation, device dislocation, device leakage, device occlusion, and vascular device infection.

Safety data are also available from 10 patients with MoCD Type A who received rcPMP in Study 3 (an observational study) [see Clinical Studies (14)]. The median time on rcPMP treatment was 1.5 years and ranged from 6 days to 4.4 years. In Study 3, the patient population was evenly distributed between males and females with a mean age of 18 days (range 1, 69) at time of first infusion, 70% were White, and 30% were Asian.

In Study 3, one patient died of necrotizing enterocolitis. Adverse reactions for the rcPMP-treated patients were similar to the NULIBRY-treated patients, except for the following additional adverse reactions that were reported in more than one patient: sepsis, oral candidiasis, varicella, fungal skin infection, and eczema.

8 USE IN SPECIFIC POPULATIONS

8.1 Pregnancy

Risk Summary

There are no available data on NULIBRY use in pregnant women to evaluate for a drug-associated risk of major birth defects, miscarriage, or adverse maternal or fetal outcomes. Animal reproduction toxicology studies have not been conducted with fosdenopterin.

The estimated background risk of major birth defects and miscarriage for the indicated population is unknown. All pregnancies have a background risk of birth defect, loss, or other adverse outcomes. In the U.S. general population, the estimated background risk of major birth defects and miscarriage in clinically recognized pregnancies are 2% to 4% and 15% to 20%, respectively.

8.2 Lactation

Risk Summary

There are no human or animal data available to assess the presence of NULIBRY or its metabolites in human milk, the effects on the breastfed infant, or the effects on milk production for the mother.

The developmental and health benefits of breastfeeding should be considered along with the mother's clinical need for NULIBRY and any potential adverse effects on the breastfed infant from NULIBRY or from the underlying maternal condition.

8.4 Pediatric Use

Safety and effectiveness of NULIBRY for the treatment of MoCD Type A have been established in pediatric patients starting from birth. Use of NULIBRY for this indication is supported by evidence from two open-label studies (Studies 1 and 2) and one observational study (Study 3), in which 13 pediatric patients aged birth to 6 years of age were treated with NULIBRY or rcPMP. Pediatric use information is discussed throughout the labeling.

Animal studies have identified that NULIBRY has phototoxic potential. Advise NULIBRY-treated patients or their caregivers to avoid patient exposure to direct sunlight and artificial UV light exposure (i.e., UVA or UVB phototherapy) and adopt precautionary measures [see Warnings and Precautions (5.1) and Nonclinical Toxicology (13.2)].

8.5 Geriatric Use

MoCD Type A is largely a disease of pediatric patients. Clinical studies of NULIBRY did not include patients 65 years of age and older.

8.6 Adult Use

The safety and effectiveness of NULIBRY for the treatment of adults with MoCD Type A have been established. Use of NULIBRY in adults for this indication is based on an adequate and well- controlled clinical investigation in pediatric patients [see Clinical Studies (14)].

11 DESCRIPTION

NULIBRY (fosdenopterin) for injection is cyclic pyranopterin monophosphate (cPMP). Fosdenopterin is present as a dihydrate of the hydrobromide salt with the chemical name (4aR,5aR,11aR,12aS)-8-amino-4a,5a,6,9,11,11a,12,12a-octahydro-2,12,12-trihydroxy-1,3,2-dioxaphosphorino[4',5':5,6]pyrano[3,2-g]pteridin-10(4H)-one 2-oxide. Fosdenopterin hydrobromide as a dihydrate is a crystalline solid. The molecular formula is C10H14N5O8P • HBr • 2H2O and the molecular weight is 480.16. The chemical structure is:

NULIBRY is supplied as a sterile, preservative-free, white to pale yellow lyophilized powder or cake in a single-dose, clear glass vial for reconstitution for intravenous infusion. Each vial contains 9.5 mg fosdenopterin (equivalent to 12.5 mg fosdenopterin hydrobromide as a dihydrate). Each vial also contains the following inactive ingredients: 10 mg ascorbic acid USP, 187.5 mg mannitol USP, and 62.5 mg sucrose NF. Sodium hydroxide NF and hydrochloric acid NF are used to adjust pH to 5.0-7.0.

12 CLINICAL PHARMACOLOGY

12.1 Mechanism of Action

Patients with MoCD Type A have mutations in the MOCS1 gene leading to deficient MOCS1A/B dependent synthesis of the intermediate substrate, cPMP. Substrate replacement therapy with NULIBRY provides an exogenous source of cPMP, which is converted to molybdopterin. Molybdopterin is then converted to molybdenum cofactor, which is needed for the activation of molybdenum-dependent enzymes, including sulfite oxidase (SOX), an enzyme that reduces levels of neurotoxic sulfites.

12.2 Pharmacodynamics

In MoCD Type A, the lack of effective SOX leads to elevated levels of the neurotoxic sulfite, S-sulfocysteine (SSC). Treatment with NULIBRY resulted in a reduction in the level of urinary SSC normalized to creatinine and the reduction was sustained with long-term treatment with NULIBRY [see Clinical Studies (14)].

Cardiac Electrophysiology

At the maximum approved recommended dose, NULIBRY did not prolong the QT interval to any clinically relevant extent.

12.3 Pharmacokinetics

The pharmacokinetics of fosdenopterin in healthy adult subjects following a single intravenous NULIBRY infusion are summarized in Table 3. The area under the plasma concentration-time curve (AUC) and the maximum plasma concentration (Cmax) of fosdenopterin increased in an approximately proportional manner with increasing doses.

Table 3 Mean (SD) Pharmacokinetic Parameters Following A Single Intravenous Dose of Fosdenopterin in Healthy Subjects
Parameter | 0.075 mg/kg^1 | 0.24 mg/kg^1 | 0.68 mg/kg^1
Cmax (ng/mL) | 285 (57) | 873 (99) | 2800 (567)
AUC0-inf (ng*h/mL) | 523 (75) | 1790 (213) | 5960 (1820)
^1 0.075 mg/kg, 0.24 mg/kg, and 0.68 mg/kg doses are 0.08, 0.27, and 0.76 times the recommended maximum dose, respectively.

Distribution

The volume of distribution (Vd) of fosdenopterin was approximately 300 mL/kg. The plasma protein binding of fosdenopterin ranged from 6 to 12%.

Elimination

The mean total body clearance (CL) of fosdenopterin ranged from 167 to 195 mL/h/kg. The mean half-life of fosdenopterin ranged from 1.2 to 1.7 hours.

Metabolism

Fosdenopterin is predominantly metabolized through nonenzymatic degradation processes to Compound Z, an inactive oxidation product of endogenous cPMP.

Excretion

Renal clearance of fosdenopterin accounts for approximately 40% of total body clearance.

Specific Populations

The effect of renal and hepatic impairment on the pharmacokinetics of fosdenopterin is unknown.

Pediatric Patients

Pharmacokinetic properties of fosdenopterin in pediatric MoCD Type A patients are similar to healthy adult subjects.

Drug Interaction Studies

In Vitro Studies

Cytochrome P450 (CYP) Enzymes: Fosdenopterin does not inhibit CYP1A2, CYP2B6, CYP2C8, CYP2C9, CYP2C19, CYP2D6, or CYP3A4/5. Fosdenopterin does not induce CYP1A2, CYP2B6, or CYP3A4.

Transporter Systems: Fosdenopterin is a weak inhibitor of MATE2-K and OAT1, but does not inhibit P-gp, BCRP, OATP1B1, OATP1B3, OCT2, OAT3, and MATE1. Fosdenopterin is a weak substrate for MATE1, but is not a substrate of P-gp, BCRP, OATP1B1, OATP1B3, OCT2, OAT1, OAT3, or MATE2-K.

13 NONCLINICAL TOXICOLOGY

13.1 Carcinogenesis, Mutagenesis, Impairment of Fertility

Carcinogenicity studies have not been conducted with fosdenopterin.

Fosdenopterin was not genotoxic in a standard battery of in vitro (bacterial reverse mutation and human lymphocyte chromosomal aberration) and in vivo (rodent bone marrow micronucleus) assays.

Fertility studies have not been conducted with fosdenopterin.

13.2 Animal Toxicology and/or Pharmacology

Fosdenopterin has demonstrated phototoxic potential in an animal study at doses equal to and greater than 4.5 times the maximum recommended human dose (based on human equivalent dose comparison). In this study, which was conducted in pigmented rats, intravenous (bolus) administration of fosdenopterin for three consecutive days followed by ultraviolet radiation (UVR) exposure resulted in dose-dependent cutaneous skin reactions (erythema, edema, flaking, and eschar) and ophthalmic and histopathologic changes indicative of phototoxicity [see Warnings and Precautions (5.1)].

14 CLINICAL STUDIES

The efficacy of NULIBRY for the treatment of patients with MoCD Type A was established based on data from three clinical studies (Studies 1, 2, and 3) that were compared to data from a natural history study.

Study 1

Study 1 (NCT02047461) was a prospective, open-label, single-arm, dose escalation study in patients with MoCD Type A who were receiving treatment with rcPMP prior to treatment with NULIBRY. Study 1 included 8 patients, 6 of whom previously participated in Study 3. The initial NULIBRY dosage was matched to the patient's rcPMP dosage upon entering the study. The NULIBRY dosage was then titrated over a period of 5 months to a maximum dosage of 0.9 mg/kg administered once daily as an intravenous infusion.

Study 2

Study 2 (NCT02629393) was a prospective, open-label, single-arm, dose escalation study in one patient with MoCD Type A who had not been previously treated with rcPMP. The initial dosage of NULIBRY in Study 2 was based on the gestational age of the patient (i.e., 36 weeks). The initial dosage was then incrementally escalated up to a maximum dosage of 0.98 mg/kg administered once daily as an intravenous infusion (1.1 times the maximum approved recommended dosage) [see Dosage and Administration (2.3)].

Study 3

Study 3 was a retrospective, observational study that included 10 patients with a confirmed diagnosis of MoCD Type A who received rcPMP. Six of these 10 patients were later enrolled in Study 1 to receive treatment with NULIBRY.

Efficacy Results

The efficacy of NULIBRY and rcPMP were assessed in a combined analysis of the 13 patients with genetically confirmed MoCD Type A from Study 1 (n=8), Study 2 (n=1), and Study 3 (n=4) who received substrate replacement therapy with NULIBRY or rcPMP.

Of the 13 treated patients included in the combined analysis, 54% were male, 77% were White and 23% were Asian; the median gestational age was 39 weeks (range 35 to 41 weeks). Of these 13 treated patients, the age at first dose was ≤ 14 days for 10 patients (with 5 patients initiating treatment at 1 day of age) and ≥ 32 days and < 69 days for the remaining 3 patients.

Overall Survival

Efficacy was assessed by comparing overall survival in pediatric patients treated with NULIBRY or rcPMP (n=13) with an untreated natural history cohort of pediatric patients with genetically confirmed MoCD Type A who were genotype-matched to the treated patients (n=18). Patients treated with NULIBRY or rcPMP had an improvement in overall survival compared to the untreated, genotype-matched, historical control group (Table 4 and Figure 1). Results were similar when comparing treated patients with all patients in the untreated natural history cohort with genetically confirmed MoCD Type A (n=37, includes the 18 genotype-matched untreated patients as well as 19 additional untreated patients who were not genotype-matched).

Table 4 Overall Survival in Patients with MoCD Type A Treated with NULIBRY or rcPMP Versus Genotype-Matched Untreated Patients in Historical Control
 | NULIBRY (or rcPMP) (n=13) | Untreated Genotype-Matched Historical Control (n=18) | Treatment Difference (95% CI)
Number of Deaths (%) | 2 (15%) | 12 (67%)
50th Percentile (Median) Survival Time in Months (95% CI)a | NE (16, NE) months | 48 (10, 99) months
Kaplan Meier Survival Probability (95% CI)
1 year | 92% (57%, 99%) | 67% (40%, 83%)
3 years | 84% (49%, 96%) | 55% (30%, 74%)
Mean Survival Time (Months)
At 1 yearb (95% CI) | 11 (9, 13) months | 10 (8, 12) months | 1 (-1, 4) months
At 3 yearsc (95% CI) | 32 (26, 37) months | 24 (17, 31) months | 8 (-1, 16) months
Hazard Ratio for Risk of Death (95% CI)d | 0.18 (0.04, 0.72)
Abbreviations: CI=confidence interval; NE=not estimable; rcPMP=recombinant Escherichia coli-derived cPMP.
a Quartile estimates from product-limit (Kaplan-Meier) method, with associated log-log confidence intervals.
b Based on the area under the survival curves up to 1 year of follow-up.
c Based on the area under the survival curves up to 3 years of follow-up.
d Based on Cox proportional hazards model regressing survival status on an indicator variable denoting treatment status. The 95% CIs are based on the modified score test statistic under the Cox model. The hazard ratio represents the risk of death in the treated patients compared to the untreated historical control patients.

Figure 1 Kaplan Meier Curve for Overall Survival in Patients with MoCD Type A Treated with NULIBRY or rcPMP Versus Genotype-Matched Untreated Patients in Historical Control

Abbreviations: rcPMP=recombinant Escherichia coli-derived cPMP

MoCD Biomarker Results

Treatment with NULIBRY resulted in a reduction in urine concentrations of SSC in patients with MoCD Type A and the reduction was sustained with long-term treatment over 48 months. The baseline level of urinary SSC normalized to creatinine was characterized in one patient (Study 2) with a value of 89.8 μmol/mmol. Following treatment with NULIBRY in Studies 1 and 2 (n=9), the mean ± SD levels of urinary SSC normalized to creatinine ranged from 11 (±8.5) to 7 (±2.4) μmol/mmol from Month 3 to Month 48.

16 HOW SUPPLIED/STORAGE AND HANDLING

How Supplied

NULIBRY (fosdenopterin) for injection is a white to pale yellow lyophilized powder or cake in a single-dose clear glass vial for reconstitution. Each NULIBRY vial contains 9.5 mg of fosdenopterin.

Each carton of NULIBRY contains one vial (NDC 73129-001-01 or 42358-295-01).

Components are not made with natural rubber latex.

Storage

Store NULIBRY frozen between -25°C and -10°C (-13°F and 14°F). Store the vial in its original carton to protect from light. For storage recommendations for the reconstituted solution [see Dosage and Administration (2.5)].

17 PATIENT COUNSELING INFORMATION

Advise patients/caregivers to read the FDA-approved patient labeling (Instructions for Use) and complete the treatment logs as appropriate.

Photosensitivity

Advise patients and/or caregivers of the potential for photosensitivity reactions and to ensure that the patient avoids or minimizes exposure to sunlight and artificial UV light exposure (i.e., UVA or UVB phototherapy) during use of NULIBRY, uses broad spectrum sunscreen with high sun protection factor (patients 6 months of age and older), and wears clothing, a hat, and sunglasses that protects against sun exposure. Instruct patients/caregivers to seek medical attention immediately if the patient develops a rash or if they notice symptoms of photosensitivity reactions (redness, burning sensation of the skin, blisters) [see Warnings and Precautions (5.1) and Nonclinical Toxicology (13.2)].

Manufactured by: Alcami Carolinas Corporation, Charleston, SC

Distributed by: Sentynl Therapeutics, Inc., Solana Beach, CA

INSTRUCTIONS FOR USE

NULIBRY® [noo lye bree]

(fosdenopterin) for injection

for intravenous use

This Instructions for Use contains information on how to prepare and give NULIBRY.

Read this Instructions for Use before you mix and give a dose of NULIBRY for the first time and each time you get a NULIBRY refill. There may be new information. This information does not take the place of talking to your healthcare provider about your child's medical condition or their treatment.

Your healthcare provider should show you the right way to mix and give your child's prescribed dose of NULIBRY before you do this for the first time.

NULIBRY is given into your child's vein (intravenously), through a special access catheter or port placed by your healthcare provider. Always follow the specific instructions given by your healthcare provider.

- If you have questions about preparing or giving NULIBRY, call Sentynl Cares | NULIBRY Patient Support Services at 1-888-251-2800.

Important information you need to know before preparing and giving NULIBRY:

- Your child's dose of NULIBRY is based on their weight. Your healthcare provider will prescribe the amount of NULIBRY needed for each dose for your child. The amount of NULIBRY needed for each dose and the number of vials needed to prepare each dose may change at each visit with your healthcare provider. The dose will be measured as the amount (volume) of solution needed in milliliters (mL).
- Keep a treatment log sheet and write down the:
  - number of vials used to prepare each dose
  - date of each dose of NULIBRY
  - lot number from each NULIBRY vial used
  - total amount (volume) of NULIBRY that was given
  - start time of the dose and the time that the dose was finished
  Be sure to keep this information up-to-date when the dose changes. Bring your treatment log sheets to each follow-up visit with your healthcare provider. Be sure to have your healthcare provider or pharmacist fill in the following information on your treatment log sheet:
- your child's dose of NULIBRY in milliliters (mL)
- number of vials needed to prepare each dose

- NULIBRY comes as a powder or cake in a vial. Each vial of NULIBRY must be mixed with Sterile Water for Injection to mix (dissolve) the powder or cake before use.
  Do not mix NULIBRY with anything other than Sterile Water for Injection.

NULIBRY must be given within 4 hours of mixing. You may keep the mixed solution of NULIBRY at room temperature or refrigerated, for up to 4 hours, until you are ready to give the dose. If you do not give the prepared dose of NULIBRY within 4 hours, all mixed medicine must be thrown away. See “How should I store NULIBRY?” below.

- Do not put NULIBRY back in the freezer after it has been mixed. Do not shake NULIBRY after it has been mixed.
- If your child misses a dose of NULIBRY, give the dose as soon as possible. Give the next scheduled dose at least 6 hours after you finish giving the missed dose.
- Avoid exposing NULIBRY to any heat source, such as a microwave or hot water.
- Do not share needles and syringes. See the section “How should I throw away (dispose of) used needles and syringes?”

How should I store NULIBRY?

Frozen vials:

- Store NULIBRY in the freezer between −13°F to 14°F (−25°C to −10°C).
- Keep NULIBRY vials in the original carton to protect from light until you are ready to use it.

Vials of NULIBRY after mixing:

- Store vials of NULIBRY that have been mixed at room temperature 59°F to 77°F (15°C to 25°C) or in the refrigerator at 36°F to 46 °F (2°C to 8°C), until you are ready to give the dose.

Vials of NULIBRY are for 1 time use only. Throw the vial away after use, even if there is medicine left in the vial. Do not save for later use. Used vials may be thrown away in your household trash.

Preparing to give NULIBRY

Step 1: Gather Supplies

- Use a clean, flat work surface.
- Remove from the freezer the NULIBRY vials needed to prepare your child's prescribed dose. You may need more than 1 vial to prepare the total amount needed for 1 dose. Allow the NULIBRY vials to reach room temperature. This can be done by rolling each vial gently between your hands for 3 to 5 minutes as shown, or by allowing the vials to sit at room temperature for about 30 minutes.

- Gather supplies needed to prepare and administer a dose of NULIBRY:
  - 1 vial of Sterile Water for Injection for each vial of NULIBRY needed for 1 dose.
    - Check the expiration date on the vial. Do not use the vial if the expiration date has passed.
    - Do not use the vial if the flip-off seal on the vial is broken or missing.
  - 1 sterile 5 mL syringe for each vial of NULIBRY needed for 1 dose to mix (dissolve) NULIBRY with Sterile Water for Injection
  - 1 sterile syringe large enough to hold the total amount of NULIBRY needed for one dose. Your healthcare provider should tell you what size and type of syringe to use.
  - sterile needles (18-gauge recommended)
  - alcohol wipes
  - 1 sharps disposal container for throwing away used needles and syringes. See “How should I throw away (dispose of) used needles, and syringes?”
  - gloves, if your healthcare provider instructs you to wear gloves when preparing and giving NULIBRY
  - 1 intravenous administration set with non-DEHP tubing and a 0.2 micron filter
  - 1 infusion pump used to give the dose of NULIBRY as instructed by your healthcare provider
  - other materials, if recommended by your healthcare provider to properly care for your child's intravenous access line or port before and after giving a dose of NULIBRY

Step 2: Wash your hands

- Wash your hands well with soap and water. Use a clean towel to dry your hands or allow them to air dry.
- If you have been told to wear gloves to prepare and give NULIBRY, put them on now.

Step 3: Prepare the vials

- Remove the flip-off cap from each vial of Sterile Water for Injection needed to prepare 1 dose.

- Clean the rubber stopper of each vial with an alcohol wipe and allow to air dry. Do not blow on the stopper to dry it faster.

Note: If you touch the vial stopper, you will need to clean it again with an alcohol wipe.

Step 4: Prepare the syringe used for drawing up Sterile Water for Injection

- Open the wrapper that contains 1 needle. Do not remove the needle cover yet.

- Open the wrapper that contains a 5 mL syringe. Attach the needle to the syringe tip with a screw action in the direction of the arrow as shown. Your needle and syringe may look different than shown.

Step 5: Fill syringe with sterile water for injection

- Remove the needle cover by pulling the cover straight off. Do not touch the needle or let the needle touch any surface.

- Hold the syringe with one hand. Use your other hand to pull back the plunger of the syringe until the top of the plunger reaches the 5 mL line on the syringe.

- Hold the vial of Sterile Water for Injection firmly on your work surface and insert the needle into the center of the vial stopper.

- Slowly turn the vial upside down. Check that the tip of the needle is not in the solution. Then, push up on the plunger to push all of the air from the syringe into the vial.

- Next, move the needle so that the tip is in the solution. Slowly pull down on the plunger of the syringe to fill the syringe with 5 mL of Sterile Water for Injection.

- Tap the syringe with your fingers until any air bubbles rise to the top of the syringe then gently push up on the plunger to push the air out of the syringe.

- After removing the air bubbles, check the syringe to be sure that 5 mL of solution is in the syringe before removing the needle from the vial.

Step 6: Mix (dissolve) NULIBRY

- Remove the flip-off cap from the vial of NULIBRY.
- Wipe the rubber stopper on the vial of NULIBRY with a new alcohol wipe.

- Hold the NULIBRY vial firmly on your work surface. Take the syringe with the Sterile Water for Injection and slowly insert the needle into the center of the vial stopper.

- Slowly push down on the plunger all the way to push the Sterile Water for Injection into the vial. Then carefully remove the needle from the vial. Throw away (dispose of) the used needle and syringe in your sharps disposal container right away. Do not try to recap the needle.
  See the section “How should I throw away (dispose of) used needles and syringes?”

- Gently swirl the vial continuously until the powder is completely dissolved. Do not shake the vial.

- Repeat steps 4 through 6 if more than 1 vial of NULIBRY is needed to prepare your child's prescribed NULIBRY dose. Use a new 5 mL syringe and new needle for each vial of NULIBRY.

Note: When mixed, the NULIBRY solution should be clear, and colorless to pale yellow.

- Do not use the solution if it is discolored or cloudy, or if there are any particles in it. If the solution is discolored or cloudy or there are particles in it:
  - Do not throw the vial away because the pharmacist may ask that you return it.
  - tell your pharmacist and ask for a replacement vial.

Step 7: Prepare a syringe with the prescribed dose of NULIBRY

- If you stored the mixed NULIBRY solution in the refrigerator, remove the vials of mixed NULIBRY solution from the refrigerator and allow them to reach room temperature. This can be done by rolling each vial gently between your hands for 3 to 5 minutes as shown, or by allowing the vials to sit at room temperature for about 30 minutes.
- Open the wrapper that contains a new sterile needle. Do not remove the needle cover yet.
- Open the wrapper that contains a sterile disposable syringe that is large enough to hold the total volume of NULIBRY needed for one dose. Attach the needle to the syringe tip with a screw action. Do not remove the needle cover yet.
- Wipe the vial stopper of each mixed NULIBRY vial with a new alcohol wipe.
- Remove the needle cover by pulling the cover straight off. Do not touch the needle or let the needle touch any surface.

- Hold the syringe with one hand. Insert the needle into the center of the NULIBRY vial stopper then slowly turn the vial upside down.

- Next, move the needle so that the tip is in the NULIBRY solution. Slowly pull back on the syringe plunger to fill the syringe with the amount of NULIBRY solution in mL for your child's prescribed dose.

- Remove any air bubbles from the syringe. Tap on the syringe barrel so that any bubbles rise to the top of the vial. Push up on the plunger to push any air bubbles back into the vial. Check to make sure that the correct amount of NULIBRY solution has been drawn into the syringe. If needed, pull down slightly on the plunger until the prescribed amount of NULIBRY solution is in the syringe.

Follow the steps below if more than 1 vial of NULIBRY is needed to make up the total amount of solution needed for 1 daily dose.

- Remove the needle and syringe from the first vial of NULIBRY. Hold the syringe with one hand. Insert the needle into the center of the next NULIBRY vial stopper then slowly turn the vial upside down.

- Next, move the needle so that the tip is in the NULIBRY solution. Slowly pull back on the syringe plunger to fill the syringe with the amount of NULIBRY solution in mL for your child's prescribed dose.

- Remove any air bubbles from the syringe. Tap on the syringe barrel so that any bubbles rise to the top of the vial. Push up on the plunger to push any air bubbles back into the vial. Then check to be sure that the prescribed amount of NULIBRY solution has been drawn into the syringe. If needed, pull down slightly on the plunger until the total prescribed amount of NULIBRY solution is in the syringe.

- Repeat this step if additional vials of NULIBRY are needed to make up your child's dose.
- When the needle is removed from the last vial of NULIBRY, all of the mixed dose of NULIBRY is in 1 syringe.

- Replace the needle cover before removing the needle from the syringe by placing the cover on a flat surface and sliding the needle into the cover as shown. With one hand, hold the syringe and use the needle to “scoop up” the cover. Once the cover is on the needle, use the other hand to secure the cover on the needle hub.

- Remove the covered needle from the syringe tip with a screw action in the direction of the arrow as shown.
- Do not touch the tip of the syringe after removing the needle.

- Throw away (dispose of) the needle in the sharps disposal container right away. See “How should I throw away (dispose of) used needles and syringes?”

- Throw away the used NULIBRY vial(s) after use, even if there is medicine left in the vial.
- The dose of NULIBRY is now ready to be given to your child.

Step 8: Giving a dose of NULIBRY

- NULIBRY is given into your child's vein (intravenously) through a special access catheter or port placed by your healthcare provider.
- When NULIBRY is given through an infusion pump, infuse NULIBRY at a rate of 1.5 mL per minute.
- If the amount (volume) in mL for your child's prescribed dose of NULIBRY is less than 2 mL, your healthcare provider may tell you to give NULIBRY by a slow intravenous push using a syringe. Follow your healthcare provider's instructions for how to give your child's dose of NULIBRY by slow intravenous push.
- Follow your healthcare provider's instructions for proper care of your child's intravenous access catheter or port before and after giving a dose of NULIBRY.

Step 9: Record the Infusion
After giving each dose of NULIBRY, record information about the dose in the treatment log sheet. See the section of this Instructions for Use called “Important information you need to know before preparing and giving NULIBRY.”

How should I throw away (dispose of) used needles and syringes?

Put your used needles and syringes in an FDA-cleared sharps disposal container right away after use.

- If you do not have an FDA-cleared sharps disposal container, you may use a household container that is:
  - made of heavy-duty plastic,
  - can be closed with a tight-fitting, puncture-resistant lid, without sharps being able to come out,
  - upright and stable during use,
  - leak-resistant, and
  - properly labeled to warn of hazardous waste inside the container.
- When your sharps disposal container is almost full, you will need to follow your community guidelines for the right way to dispose of your sharps disposal container. There may be state or local laws about how you should throw away used needles and syringes. For more information about safe sharps disposal, and for specific information about sharps disposal in the state that you live in, go to the FDA's website at: http://www.fda.gov/safesharpsdisposal
- Do not dispose of your used sharps disposal container in your household trash unless your community guidelines permit this. Do not recycle your used sharps disposal container.
- Keep the sharps disposal container out of the reach of children.

What should I avoid during treatment with NULIBRY?

NULIBRY may cause skin reactions.

- Limit or avoid your child's exposure or time in sunlight and artificial ultraviolet (UV) light, such as UVA or UVB phototherapy.
- Your child should wear clothing, a hat, and sunglasses that protect against sun exposure.
- If your child is 6 months of age or older apply a broad spectrum sunscreen with high sun protection factor.

Get medical help right away if your child develops a rash, or if you notice symptoms of a skin reaction, including: skin redness, blisters, or if your child feels like their skin is burning.

What are the ingredients in NULIBRY?

Active ingredient: fosdenopterin

Inactive ingredients: ascorbic acid, mannitol, sucrose. Sodium hydroxide and hydrochloric acid are used to adjust the pH.

For more information, call 1-888-507-5206 or go to www.NULIBRY.com.

Manufactured by:
Alcami Carolinas Corporation
Charleston, SC

Distributed by:
Sentynl Therapeutics, Inc.
Solana Beach, CA

This Instructions for Use has been approved by the U.S. Food and Drug Administration.
Issued: 10/2022

Principal Display Panel – 9.5 mg Carton Label

NDC 42358-295-01

Nulibry®

(fosdenopterin)
for injection

9.5 mg/vial

For intravenous
infusion only

Contains 1 vial
Single-dose vial

Reconstitute prior to use

Discard unused portion

Rx only